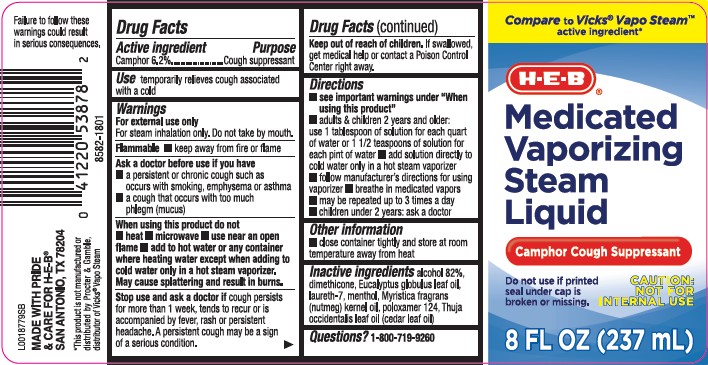 DRUG LABEL: Vaproizing
NDC: 37808-397 | Form: LIQUID
Manufacturer: H E B
Category: otc | Type: HUMAN OTC DRUG LABEL
Date: 20260224

ACTIVE INGREDIENTS: CAMPHOR (NATURAL) 62 mg/1 mL
INACTIVE INGREDIENTS: ALCOHOL; DIMETHICONE; EUCALYPTUS OIL; LAURETH-7; MENTHOL; NUTMEG OIL; POLOXAMER 124; CEDAR LEAF OIL

HEB 397.002/397AA rev 2-AB
Medicated Vaporizing Steam Liquid

warning

Failure to follow these warnings could result in serious consequences

Active ingredient

Camphor 6.2%

Purpose

Cough suppressant

Use

temporarily relieves cough associated with a cold

Warnings

For external use only

For steam inhalation only. Do not take by mouth.

Flammable

- keep away from fire or flame

Ask a doctor before use

- a persistent or chronic cough such as occurs with smoking, emphysema or asthma
- a cough that occurs with too much phlegm (mucus)

When using this product do not

- heat
- microwave
- use near an open flame
- add to hot water or any container where heating water except when adding to cold water only in a hot steam vaporizer. May cause splattering and result in burns.

Stop use and ask a doctor if

cough persists more than 1 week, tends to recur or is accompanied by fever, rash or persistent headache. A persistent cough may be a sign of a serious condition.

Keep out of reach of children.

If swallowed, get medical help or contact a Poison Control Center right away.

Directions

- see important warnings under "When using this product"
- adults & children 2 years of age and older: use 1 tablespoon of solution for each quart of water or 1 1/2 teaspoons of solution for each pint of water
- add solution directly to cold water only in a hot steam vaporizer
- follow manufacture's directions for using vaporizer
- breathe in medicated vapors
- may be repeated up to 3 times a day
- children under 2 years: ask a doctor

other information

- close container tightly and store at room temperature away from heat

Inactive ingredients

alcohol 82%, dimethicone, eucalyptus globulus leaf oil, laureth-7, menthol, Myristica fragrans (nutmeg) kernel oil, poloxamer 124, Thuja occidentalis leaf oil (cedar leaf oil)

Questions?

1-800-719-9260

Disclaimer

*This product is not manufactured or distributed by Procter & Gamble, distributor of VicksVapo Steam.

Adverse Reactions Section

Made with Pride & Care for H E B®

San Antinio, TX 78204

principal display panel

Compare to Vicks®Vapo Steam™ active ingredient*

H-E-B®

MEDICATED VAPORIING STEAM LIQUID

Camphor Cough Suppressant

Do not use if printed seal under cap is broken or mssing.

CAUTION: NOT FOR INTERNAL USE

8 FL OZ (237 mL)